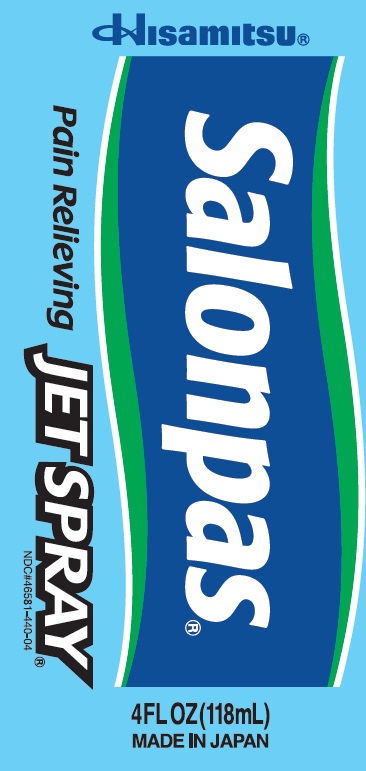 DRUG LABEL: Salonpas pain relieving JET
NDC: 46581-440 | Form: AEROSOL, SPRAY
Manufacturer: Hisamitsu Pharmaceutical Co., Inc.
Category: otc | Type: HUMAN OTC DRUG LABEL
Date: 20251215

ACTIVE INGREDIENTS: MENTHOL 3.0 g/100 g; METHYL SALICYLATE 10.0 g/100 g
INACTIVE INGREDIENTS: ALCOHOL

Active ingredients

Menthol 3%

Methyl salicylate 10%

Purpose

Topical analgesic

Uses

For temporary relief of minor aches and pains of muscles and joints associated with:

- strains
- sprains
- bruises
- simple backache
- arthritis

Warnings

For external use only

Allergy alert:

If prone to allergic reaction from aspirin or salicylates, consult a doctor before use.

Flammable:

- keep away from fire or flame
- do not use where sparks come out
- do not use in a confined space
- do not puncture or incinerate container. Contents under pressure.
- do not expose to temperature exceeding 120 degrees F (48 degrees C)

Do not use

- on wounds or damaged skin
- with a heating pad
- if you are allergic to any ingredients of this product

When using this product

- use only as directed
- avoid contact with the eyes, mucous membranes or rashes
- do not bandage tightly
- avoid inhalation

Stop use and ask a doctor if

- skin reactions such as redness, itching, rash, excessive irritation, burning sensation, swelling or blistering occur
- conditions worsen
- symptoms persist for more than 7 days
- symptoms clear up and occur again within a few days

If pregnant or breast-feeding,

ask a health professional before use.

Keep out of reach of children.

If swallowed, get medical help or contact a Poison Control Center right away.

Directions

Adults and children 12 years of age and over:

- shake the can very well before use
- to avoid frostbite, hold the can 4 inches (10 cm) away from the skin, and spray each affected area for no longer than 1 second
- apply to affected area not more than 3 to 4 times daily

Children under 12 years of age: consult a docutor

Other information

- Avoid storing product in direct sunlight and heat

Inactive ingredient

alcohol

Questions or comments?

Toll free 1-800-826-8861

www.salonpas.us

Principal Display Panel

Hisamitsu

Salonpas Pain Relieving JET SPRAY

NDC#46581-440-04

4 FL OZ (118mL)

MADE IN JAPAN